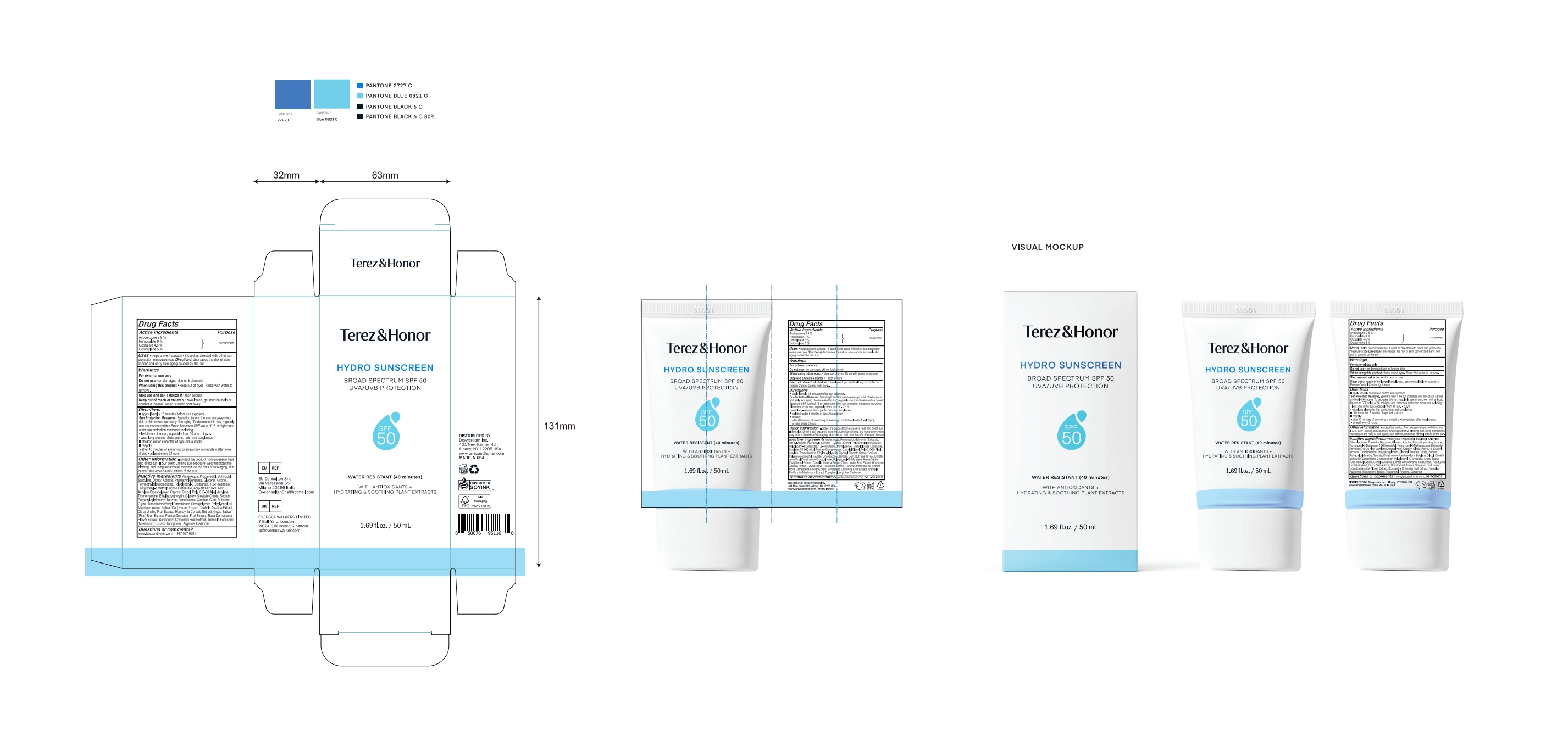 DRUG LABEL: Terez Honor Hydro Sunscreen
NDC: 87167-150 | Form: CREAM
Manufacturer: DEWYCREAM INC
Category: otc | Type: HUMAN OTC DRUG LABEL
Date: 20251019

ACTIVE INGREDIENTS: HOMOSALATE 4.5 g/50 mL; AVOBENZONE 1.45 g/50 mL; OCTISALATE 2.25 g/50 mL; OCTOCRYLENE 2.5 g/50 mL
INACTIVE INGREDIENTS: WATER; PROPANEDIOL; DIBUTYL ADIPATE; SODIUM POLYACRYLOYLDIMETHYL TAURATE; TANGERINE; TOCOPHEROL; ARGININE; OAT; POLYGLYCERYL-3 DISTEARATE; CENTELLA ASIATICA TRITERPENOIDS; 1,2-HEXANEDIOL; GLYCERYL STEARATE CITRATE; BUTYLENE GLYCOL; BUTYLOCTYL SALICYLATE; GLYCERIN; TROMETHAMINE; ETHYLHEXYLGLYCERIN; XANTHAN GUM; CARBOMER HOMOPOLYMER, UNSPECIFIED TYPE; ROSA DAMASCENA FLOWER; HOUTTUYNIA CORDATA FLOWERING TOP; ALCOHOL; CAPRYLYL GLYCOL; POMEGRANATE; POLYGLYCERYL-3 METHYLGLUCOSE DISTEARATE; DIMETHICONE; POLYGLYCERYL-10 MYRISTATE; RICE BRAN; PHENETHYL BENZOATE; POLYMETHYLSILSESQUIOXANE (4.5 MICRONS)

Active Ingredients

Avobenzone 2.9 %
Homosalate 9 %
Octisalate 4.5 %
Octocrylene 5 %

Purpose

sunscreen

Uses

helps prevent sunburn • if used as directed with other sun

protection measures (see Directions) decreases the risk of skin

cancer and early skin aging caused by the sun

Warnings

For external use only

Do not use

• on damaged skin or broken skin

When using this product

• keep out of eyes. Rinse with water to remove.

Stop use

and ask a doctor if • rash occurs

Keep out of reach of children

If swallowed, get medical help or contact a Poison Control Center right away.

Directions

■ apply liberally 15 minutes before sun exposure.

Sun Protection Measures. Spending time in the sun increases your risk of skin cancer and early skin aging. To decrease this risk, regularly use a sunscreen with a Broad Spectrum SPF value of 15 or higher and other sun protection measures including:

• limit time in the sun, especially from 10 a.m. - 2 p.m.

• wear long-sleeved shirts, pants, hats, and sunglasses

■ children under 6 months of age: Ask a doctor

■ reapply at least every 2 hours

■ use a water-resistant sunscreen if swimming or sweating

• after 40 minutes of swimming or sweating • immediately after towel drying • at least every 2 hours

Other information

■ protect the product from excessive heat and direct sun ■ Sun alert: Limiting sun exposure, wearing protective clothing, and using sunscreens may reduce the risks of skin aging, skin cancer, and other harmful effects of the sun.

Inactive ingredients

Water/Aqua, Propanediol, Butyloctyl Salicylate, Dibutyl Adipate, Phenethyl Benzoate, Glycerin, Alcohol, Polymethylsilsesquioxane, Polyglyceryl-3 Distearate, 1,2-Hexanediol, Polyglyceryl-3 Methylglucose Distearate, Acrylates/C10-30 Alkyl Acrylate Crosspolymer, Caprylyl Glycol, Poly C10-30 Alkyl Acrylate, Tromethamine, Ethylhexylglycerin, Glyceryl Stearate Citrate, Sodium Polyacryloyldimethyl Taurate, Dimethicone, Xanthan Gum, Butylene Glycol, Dimethicone/Vinyl Dimethicone Crosspolymer, Polyglyceryl-10 Myristate, Avena Sativa (Oat) Kernel Extract, Centella Asiatica Extract, Citrus Unshiu Fruit Extract, Houttuynia Cordata Extract, Oryza Sativa (Rice) Bran Extract, Punica Granatum Fruit Extract, Rosa Damascena Flower Extract, Schisandra Chinensis Fruit Extract, Tremella Fuciformis (Mushroom) Extract, Tocopherol, Arginine, Carbomer

Questions or comments?

www.terezandhoner.com, 1-917-587-9381